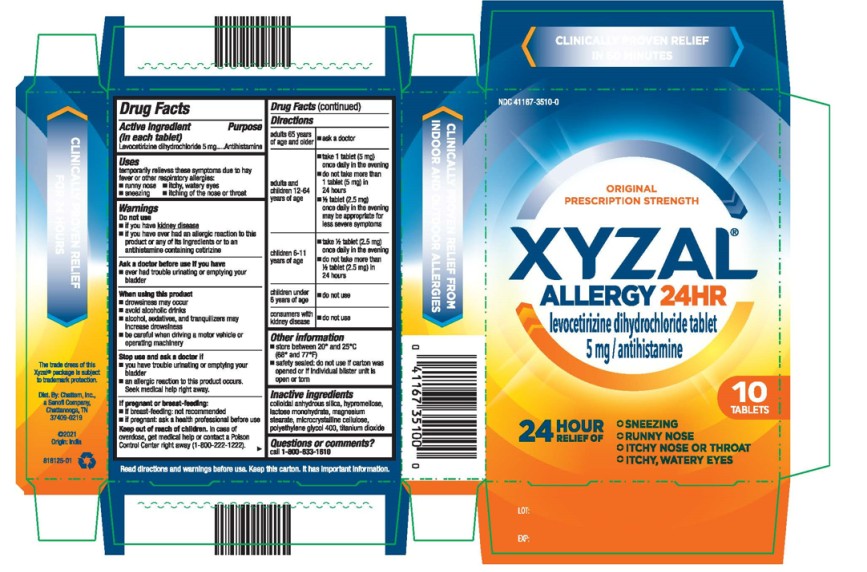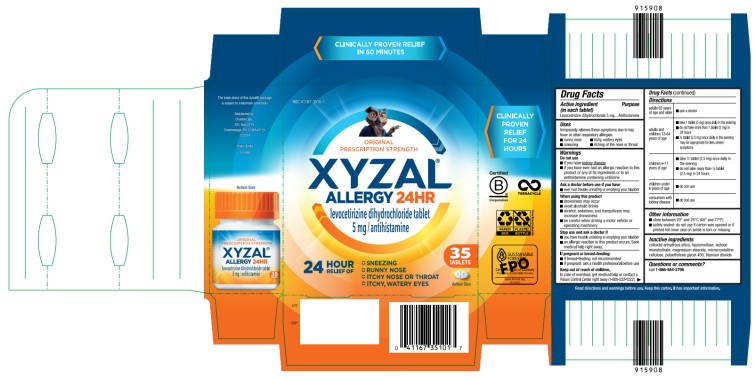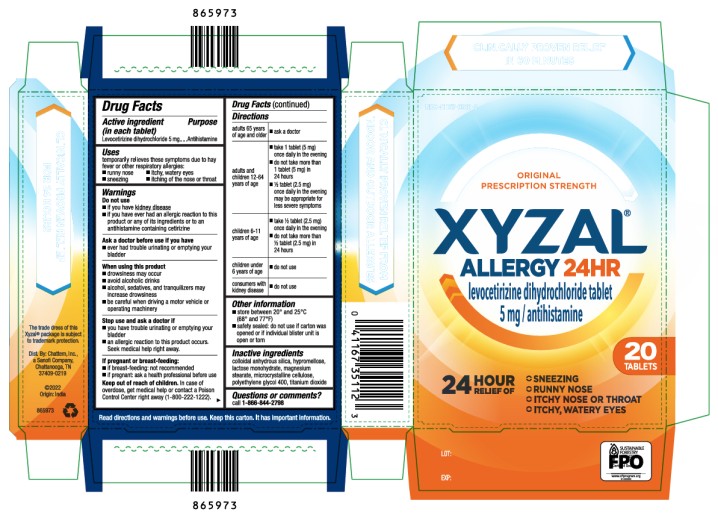 DRUG LABEL: Xyzal Allergy 24HR
NDC: 41167-3510 | Form: TABLET
Manufacturer: Chattem, Inc.
Category: otc | Type: HUMAN OTC DRUG LABEL
Date: 20250101

ACTIVE INGREDIENTS: LEVOCETIRIZINE DIHYDROCHLORIDE 5 mg/1 1
INACTIVE INGREDIENTS: SILICON DIOXIDE; HYPROMELLOSES; LACTOSE MONOHYDRATE; MAGNESIUM STEARATE; MICROCRYSTALLINE CELLULOSE; POLYETHYLENE GLYCOL 400; TITANIUM DIOXIDE

Xyzal Allergy 24HR

Xyzal Allergy 24HR Tablet

Drug Facts

Active ingredient

(in each tablet)

Levocetirizine dihydrochloride 5 mg

Purpose

Antihistamine

Uses

temporarily relieves these symptoms due to hay fever or other respiratory allergies:

- runny nose
- sneezing
- itchy, watery eyes
- itching of the nose or throat

Warnings

Do not use

- if you have kidney disease
- if you have ever had an allergic reaction to this product or any of its ingredients or to an antihistamine containing cetirizine

Ask a doctor before use if you have

- ever had trouble urinating or emptying your bladder

When using this product

- drowsiness may occur
- avoid alcoholic drinks
- alcohol, sedatives, and tranquilizers may increase drowsiness
- be careful when driving a motor vehicle or operating machinery

Stop use and ask a doctor if

- you have trouble urinating or emptying your bladder
- an allergic reaction to this product occurs. Seek medical help right away.

If pregnant or breast-feeding:

- if breast-feeding: not recommended
- if pregnant: ask a health professional before use

Keep out of reach of children.

In case of overdose, get medical help or contact a Poison Control Center right away (1-800-222-1222).

Directions

adults 65 years of age and older | ■ ask a doctor
adults and children 12-64 years of age | ■ take 1 tablet (5 mg) once daily in the evening ■ do not take more than 1 tablet (5 mg) in 24 hours ■ ½ tablet (2.5 mg) once daily in the evening may be appropriate for less severe symptoms
children 6-11 years of age | ■ take ½ tablet (2.5 mg) once daily in the evening ■ do not take more than ½ tablet (2.5 mg) in 24 hours
children under 6 years of age | ■ do not use
consumers with kidney disease | ■ do not use

Other information

- store between 20° and 25°C (68° and 77°F)
- (if blister) safety sealed: do not use if carton was opened or if individual blister unit is open or torn

(if bottled) safety sealed: do not use if carton was opened or if printed foil inner seal on bottle is torn or missing

(if stretch card) safety sealed: do not use if sealed package was torn or opened, or if printed foil inner seal on bottle is torn or missing

Inactive ingredients

Colloidal anhydrous silica, hypromellose, lactose monohydrate, magnesium stearate, microcrystalline cellulose, polyethylene glycol 400, titanium dioxide

Questions or comments?

call 1-800-633-1610

PRINCIPAL DISPLAY PANEL

NDC 41167-3510-0
XYZAL
Allergy 24HR
5 mg
10 Tablets

PRINCIPAL DISPLAY PANEL

NDC 41167-3510-1
XYZAL
Allergy 24HR
5 mg
35 Tablets

PRINCIPAL DISPLAY PANEL

NDC 41167-3511-2
XYZAL
Allergy 24HR
5 mg
20 Tablets